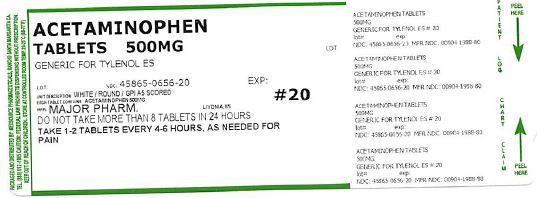 DRUG LABEL: Extra Strength Mapap
NDC: 45865-656 | Form: TABLET
Manufacturer: Medsource Pharmaceuticals
Category: otc | Type: HUMAN OTC DRUG LABEL
Date: 20180727

ACTIVE INGREDIENTS: ACETAMINOPHEN 500 mg/1 1
INACTIVE INGREDIENTS: POVIDONE, UNSPECIFIED; STARCH, CORN; SODIUM STARCH GLYCOLATE TYPE A CORN; STEARIC ACID

Drug Facts

Active ingredient (in each tablet)

Acetaminophen 500 mg

Purposes

Pain Reliever/Fever Reducer

Aspirin Free Extra Strength Pain Reliever

Uses

for the temporary relief of minor aches and pains due to:

- headache
- muscular aches
- backache
- minor pain of arthritis
- the common cold
- toothache
- premenstrual and menstrual cramps
- temporarily reduces fever

Warnings

Liver warning: This product contains acetaminophen.

The maximum daily dose of this product is 6 tablets (3,000mg) in 24 hours. Severe liver damage may occur if you take

- more than 4,000 mg of acetaminophen in 24 hours
- with other drugs containing acetaminophen
- 3 or more alcoholic drinks every day while using this product

Do not use

- with any other drug containing acetaminophen (prescription or non prescription). If you are not sure whether a drug contains acetaminophen, ask a doctor or pharmacist.
- if you are allergic to acetaminophen or any of the inactive ingredients in this product

Ask a doctor before use if you have

liver disease.

Ask a doctor or pharmacist before use if you are

taking the blood thinning drug warfarin.

Stop use and ask a doctor if

- pain gets worse or lasts more than 10 days
- fever gets worse or lasts more than 3 days
- new symptoms occur
- redness or swelling is present

These could be signs of a serious condition.

PREGNANCY OR BREAST FEEDING

If pregnant or breast-feeding, ask a health professional before use.

Keep out of reach of children

This Unit Dose package is not child resistant and is Intended for Institutional Use Only.

OVERDOSAGE

Overdose warning: Taking more than the recommended dose (overdose) may cause liver damage. In the case of overdose, get medical help or contact a Poison Control Center right away (1-800-222-1222). Quick medical attention is critical for adults as well as for children even if you do not notice any signs or symptoms.

Directions

Do not take more than the directed (see overdose warning)

Adults and children 12 years and over:

- Take 2 tablets every 6 hours while symptoms last.
- Do not take more than 6 tablets in 24 hours unless directed by a doctor
- Do not take for more than 10 days unless directed by a doctor

Children under 12 years: Do not use adult Extra Strength product in children under 12 years of age; this will provide more than the recommended dose (overdose) of acetaminophen and may cause liver damage.

Other information

- Store at room temperature

Inactive ingredients

Povidone, Pregelatinized Starch, Sodium Starch Glycolate, Stearic Acid